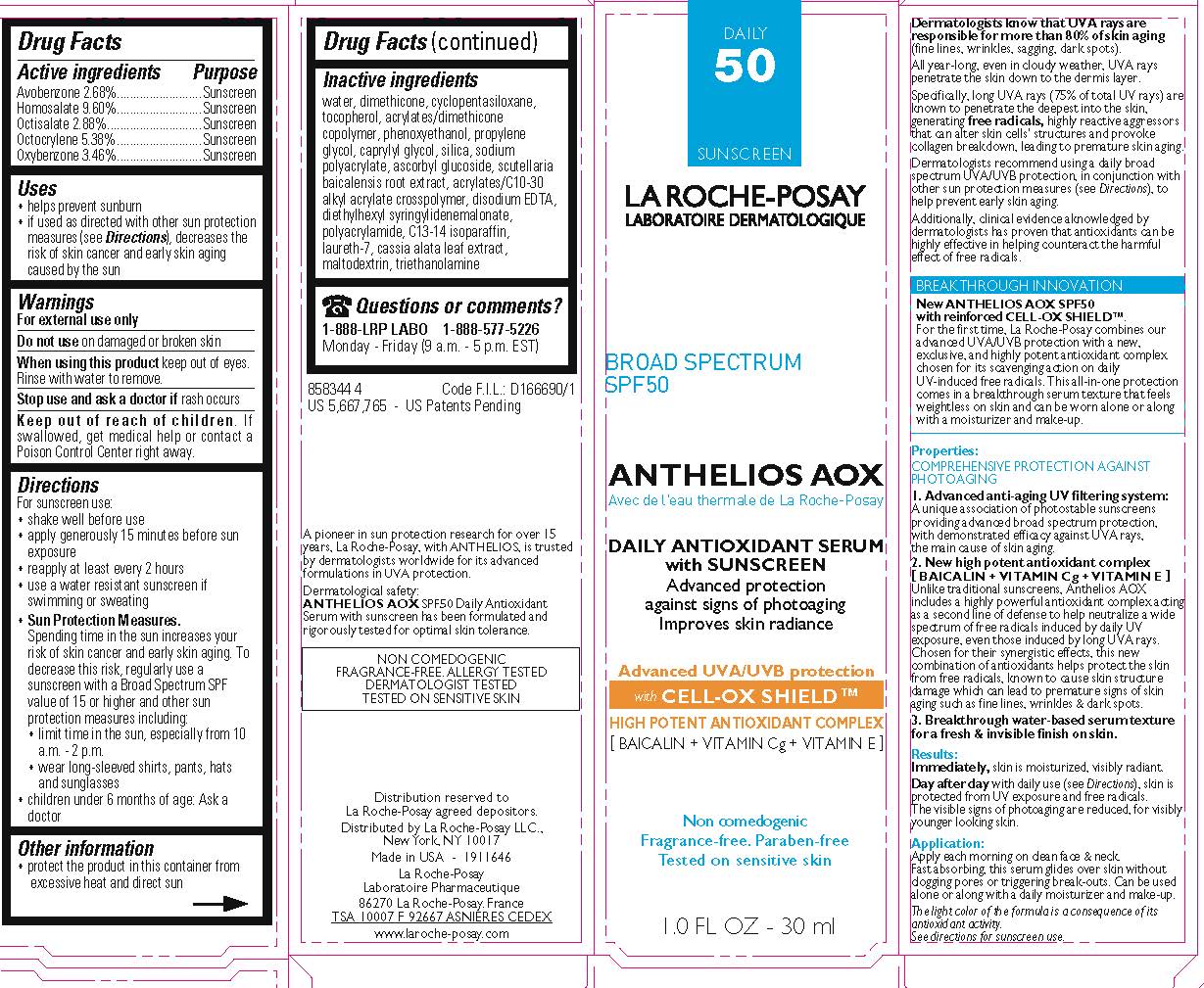 DRUG LABEL: La Roche Posay Laboratoire Dermatologique Anthelios AOX Daily Antioxidant Serum Broad Spectrum SPF 50 Sunscreen
NDC: 49967-370 | Form: LOTION
Manufacturer: L'Oreal USA Products Inc
Category: otc | Type: HUMAN OTC DRUG LABEL
Date: 20231231

ACTIVE INGREDIENTS: AVOBENZONE 26.8 mg/1 mL; HOMOSALATE 96 mg/1 mL; OCTISALATE 28.8 mg/1 mL; OCTOCRYLENE 53.8 mg/1 mL; OXYBENZONE 34.6 mg/1 mL
INACTIVE INGREDIENTS: WATER; DIMETHICONE; TOCOPHEROL; PHENOXYETHANOL; PROPYLENE GLYCOL; CAPRYLYL GLYCOL; ASCORBYL GLUCOSIDE; LAURETH-7; MALTODEXTRIN

Drug Facts

Active ingredient

Avobenzone 2.68%

Homosalate 9.6%

Octisalate 2.88%

Octocrylene 5.38%

Oxybenzone 3.46%

Purpose

Sunscreen

Uses

- helps prevent sunburn
- if used as directed with other sun protection measures (see Directions), decreases the risk of skin cancer and early skin aging caused by the sun

Warnings

For external use only

Do not use

on damaged or broken skin

When using this product

keep out of eyes. Rinse with water to remove.

Stop use and ask a doctor if

rash occurs

Keep out of reach of children.

If swallowed, get medical help or contact a Poison Control Center right away.

Directions

For sunscreen use:

- shake well before use
- apply generously 15 minutes before sun exposure
- reapply at least every 2 hours
- use a water resistant sunscreen if swimming or sweating
- Sun Protection Measures. Spending time in the sun increases your risk of skin cancer and early skin aging. To decrease this risk, regularly use a sunscreen with a Broad Spectrum SPF value of 15 or higher and other sun protection measures including:

● limit time in the sun, especially from 10 a.m. – 2 p.m.

● wear long-sleeved shirts, pants, hats, and sunglasses

- children under 6 months of age: Ask a doctor

Other information

protect the product in this container from excessive heat and direct sun

Inactive ingredients

water, dimethicone, cyclopentasiloxane, tocopherol, acrylates/dimethicone copolymer, phenoxyethanol, propylene glycol, caprylyl glycol, silica, sodium polyacrylate, ascorbyl glucoside, scutellaria baicalensis root extract, acrylates/C10-30 alkyl acrylate crosspolymer, disodium EDTA, diethylhexyl syringylidenemalonate, polyacrylamide, C13-14 isoparaffin, laureth-7, cassia alata leaf extract, maltodextrin, triethanolamine

Questions or comments?

1-888-LRP-LABO 1-888-577-5226

Monday - Friday (9 a.m. - 5 p.m. EST)